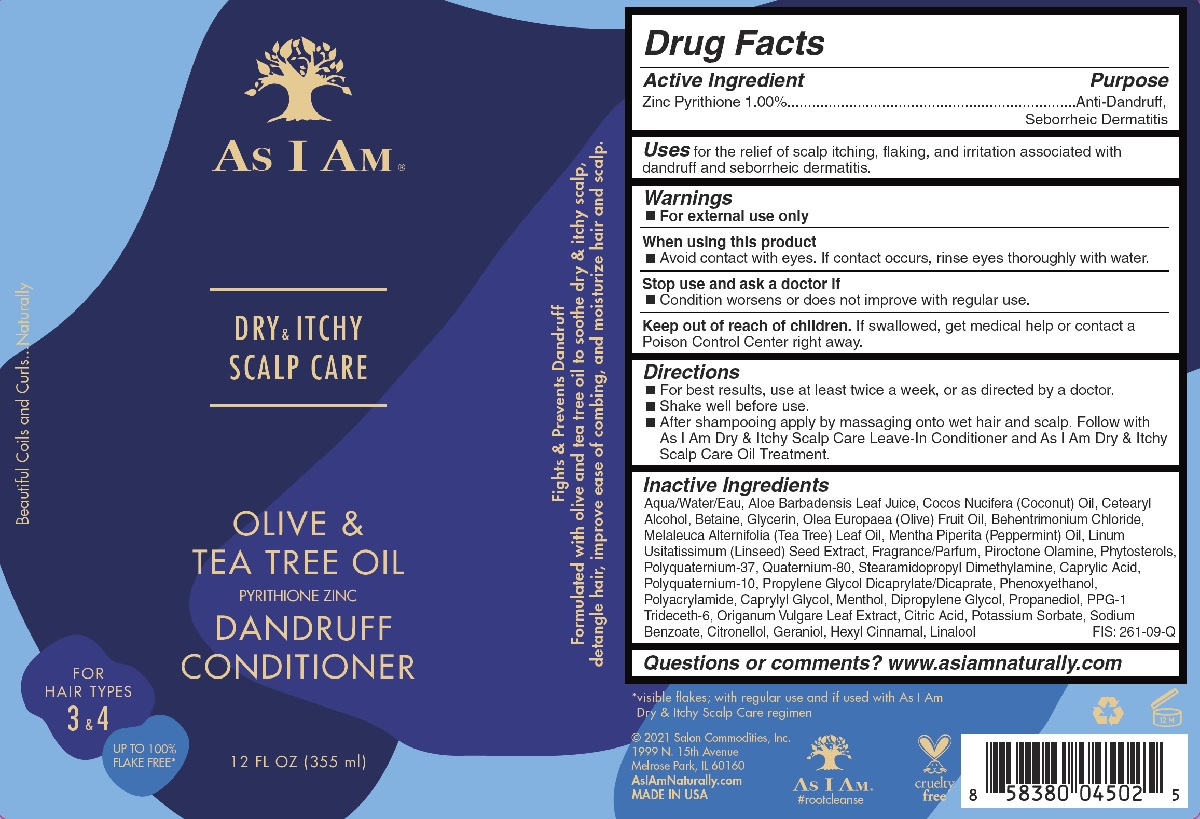 DRUG LABEL: As I Am
NDC: 72474-101 | Form: LOTION
Manufacturer: Salon Commodities, Inc.
Category: otc | Type: HUMAN OTC DRUG LABEL
Date: 20241009

ACTIVE INGREDIENTS: PYRITHIONE ZINC 10 mg/1 mL
INACTIVE INGREDIENTS: SODIUM BENZOATE; BEHENTRIMONIUM CHLORIDE; 2-(CYCLOHEXYLAMINO)ETHANESULFONIC ACID; WATER; ALOE VERA LEAF; PPG-1 TRIDECETH-6; OREGANO; CITRIC ACID MONOHYDRATE; .BETA.-CITRONELLOL, (R)-; .ALPHA.-HEXYLCINNAMALDEHYDE; PROPANEDIOL; CAPRYLYL GLYCOL; COCONUT OIL; GERANIOL; LINALOOL, (+/-)-; CETOSTEARYL ALCOHOL; BETAINE; GLYCERIN; OLIVE OIL; TEA TREE OIL; PEPPERMINT OIL; .BETA.-SITOSTEROL; POLYQUATERNIUM-37 (10000 MPA.S); LINSEED OIL; PIROCTONE OLAMINE; STEARAMIDOPROPYL DIMETHYLAMINE; CAPRYLIC ACID; POLYQUATERNIUM-10 (1000 MPA.S AT 2%); PROPYLENE GLYCOL DICAPRYLATE/DICAPRATE; PHENOXYETHANOL; POLYACRYLAMIDE (10000 MW); MENTHOL; DIPROPYLENE GLYCOL; POTASSIUM SORBATE

As I Am - Dry & Itchy Scalp Care - Olive and Tea Tree Oil Conditioner

Active Ingredient

Zinc Pyrithione 1%

Purpose

Anti-Dandruff, Seborrheic Dermatitis

Uses

For the relief of scalp itching, flaking, and irritation associated with dandruff and seborrheic dermatitis.

Warnings

- For external use only.

When Using This Product

- Avoid contact with eyes. If contact occurs, rinse eyes thoroughly with water.

Stop use and ask a doctor if

- Condition worsens or does not improve with regular use.

Keep out of reach of children. If swallowed, get medical help or contact a Poison Control Center right away.

Directions

- For best results, use at least twice a week, or as directed by a doctor.
- Shake well before use.
- After shampooing apply by massaging onto wet hair and scalp. Follow with As I Am Dry & Itchy Scalp Care Leave-In Conditioner and As I Am Dry & Itchy Scalp Care Oil Treatment.

Inactive Ingredient

Aqua/Water/Eau, Aloe Barbadensis Leaf Juice, Cocos Nucifera (Coconut) Oil, Cetearyl

Alcohol, Betaine, Glycerin, Olea Europaea (Olive) Fruit Oil, Behentrimonium Chloride,

Melaleuca Alternifolia (Tea Tree) Leaf Oil, Mentha Piperita (Peppermint) Oil, Linum

Usitatissimum (Linseed) Seed Extract, Fragrance/Parfum, Piroctone Olamine, Phytosterols,

Polyquaternium-37, Quaternium-80, Stearamidopropyl Dimethylamine, Caprylic Acid,

Polyquaternium-10, Propylene Glycol Dicaprylate/Dicaprate, Phenoxyethanol,

Polyacrylamide, Caprylyl Glycol, Menthol, Dipropylene Glycol, Propanediol, PPG-1

Trideceth-6, Origanum Vulgare Leaf Extract, Citric Acid, Potassium Sorbate, Sodium

Benzoate, Citronellol, Geraniol, Hexyl Cinnamal, Linalool

Questions or comments? www.asiamnaturally.com

PACKAGE LABEL

As I Am - Dry & Itchy Scalp Care - Olive and Tea Tree Oil Conditioner

12 FL OZ (355 ml)

NDC 72474-101-01